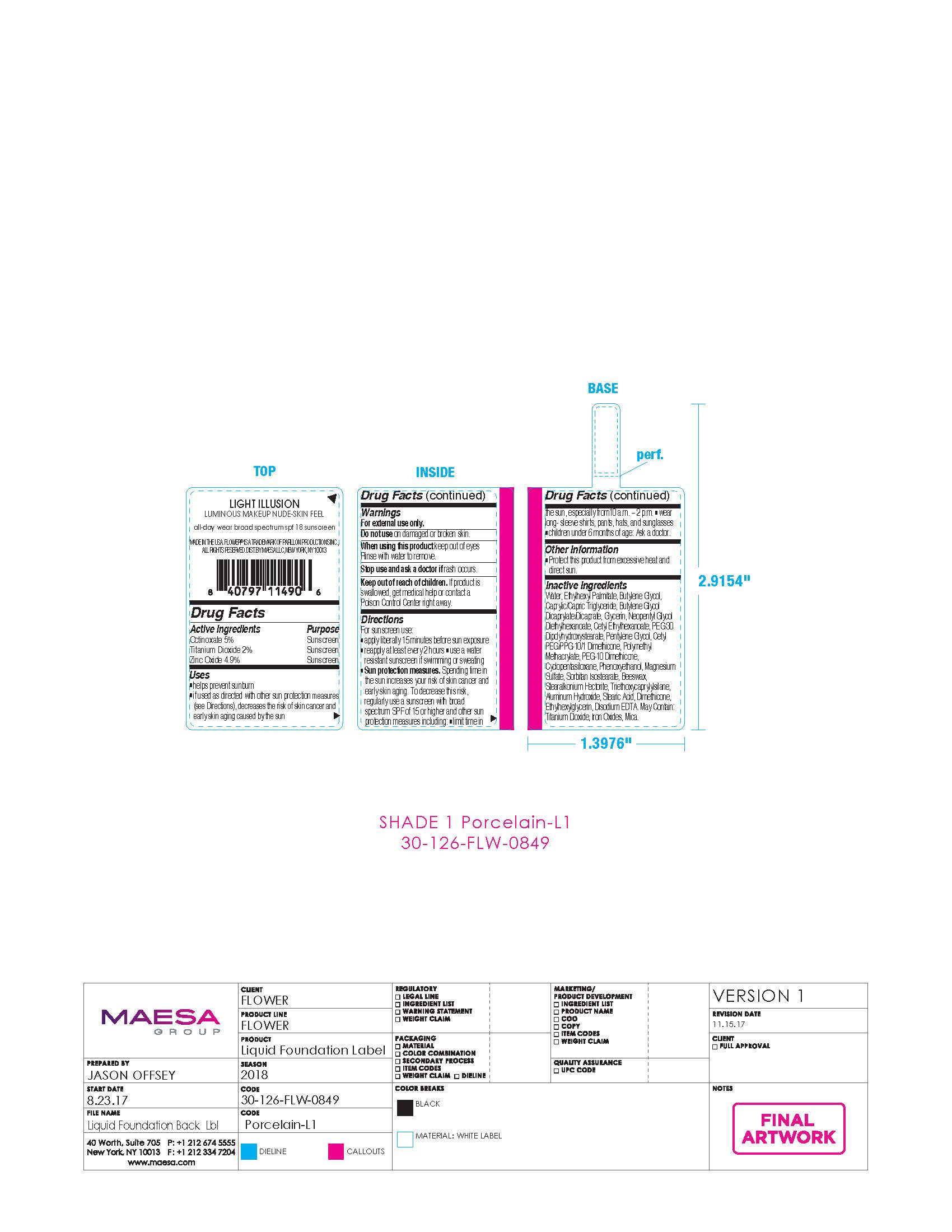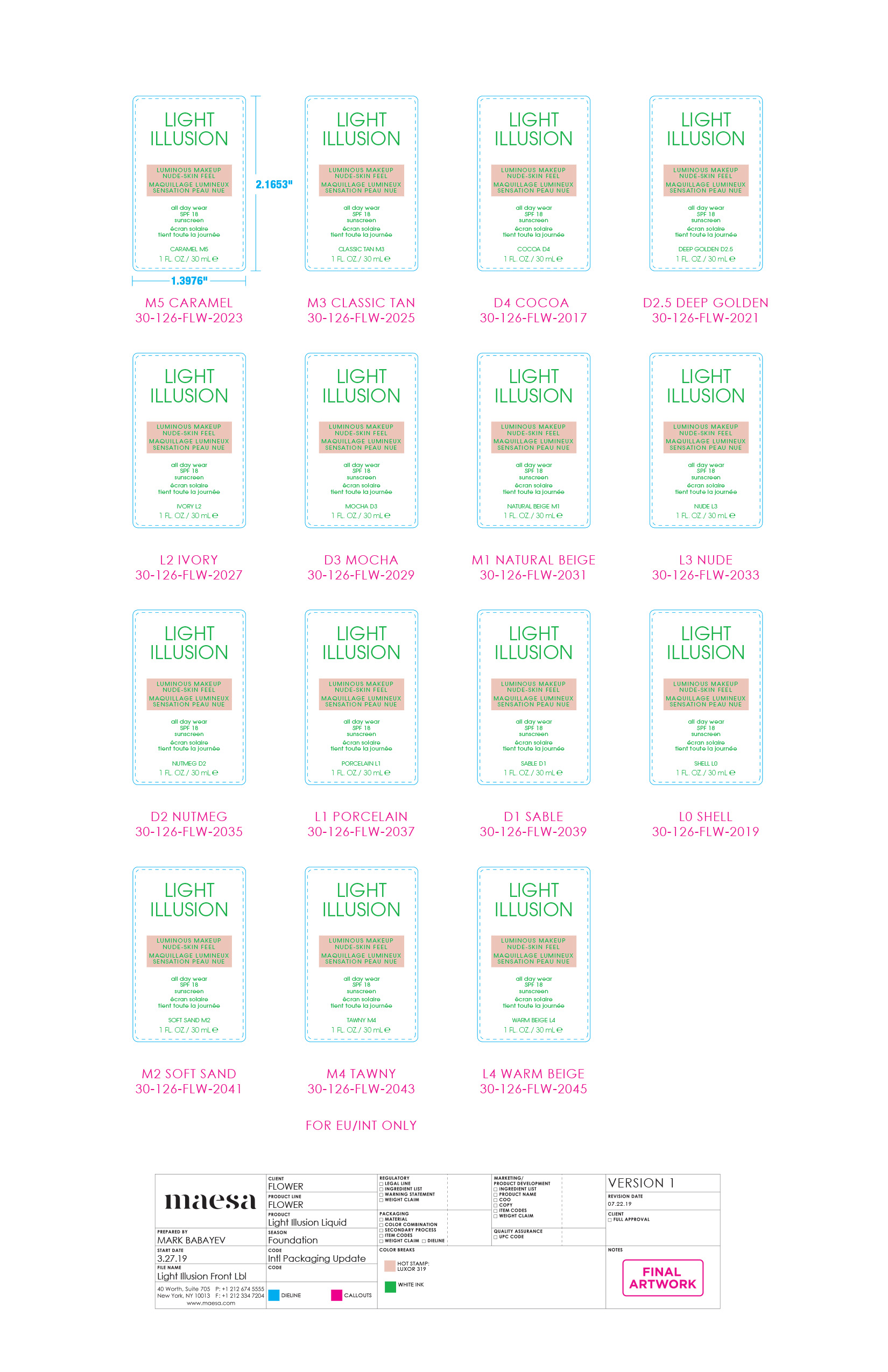 DRUG LABEL: Light Illusion Luminous Makeup Nude-Skin Feel SPF18 PORCELAIN
NDC: 68577-175 | Form: CREAM
Manufacturer: COSMAX USA, INC
Category: otc | Type: HUMAN OTC DRUG LABEL
Date: 20241219

ACTIVE INGREDIENTS: ZINC OXIDE 4.9 mg/100 mg; TITANIUM DIOXIDE 2 mg/100 mg; OCTINOXATE 5 mg/100 mg
INACTIVE INGREDIENTS: WATER; ETHYLHEXYL PALMITATE; BUTYLENE GLYCOL; NEOPENTYL GLYCOL DIETHYLHEXANOATE; CAPRYLIC/CAPRIC TRIGLYCERIDE; STEARALKONIUM HECTORITE; ETHYLHEXYLGLYCERIN; BUTYLENE GLYCOL DICAPRYLATE/DICAPRATE; POLY(METHYL METHACRYLATE; 450000 MW); GLYCERIN; PHENOXYETHANOL; MAGNESIUM SULFATE; SORBITAN ISOSTEARATE; STEARIC ACID; DIMETHICONE; CETYL PEG/PPG-10/1 DIMETHICONE (HLB 3); PEG-10 DIMETHICONE (600 CST); BEESWAX; ALUMINUM HYDROXIDE; PENTYLENE GLYCOL; TRIETHOXYCAPRYLYLSILANE; EDETATE DISODIUM; CYCLOPENTASILOXANE; FERROUS OXIDE; MICA

FLOWER Light Illusion Luminous Makeup Nude- Skin Feel SPF 18- PORCELAIN

Active Ingredients

Octinoxate 5%

Titanium Dioxide 2%

Zinc Oxide 4.9%

Purpose

Sunscreen

USES

- helps prevent sunburn
- if used as directed with other sun protection measures (see Directions), decreases the risk of skin cancer and early skin aging caused by the sun

WARNINGS

For external use only.

Do not useon damaged or broken skin

WHEN USING

When using this productkeep out of eyes. Rinse with water to remove.

Stop use and ask a doctor ifrash occurs

Keep out of reach of children.If product is swallowed, get medical help or contact a Poison Control Center right away.

DIRECTIONS

Drections

For sunscreen use:

- Apply liberally 15 minutes before sun exposure
- reapply at least every 2 hours
- use a water resistant sunscreen if swimming or sweating
- Sun protection measures.Spending time in the sun increases your risk of skin cancer and early skin aging. To decrease this risk, regularly use a sunscreen with broad spectrum SPF of 15 or higher and other sun protection measures including:
- limit time in the sun, especially from 10 a.m. - 2 p.m.
- wear long-sleeve shirts, pants, hats, and sunglasses
- children under 6 months of age: Ask a doctor

OTHER INFORMATION

- Protect this product from excessive heat and direct sun

INACTIVE INGREDIENT

Inactive ingredients:Water, Ethylhexyl Palmitate, Butylene Glycol, Caprylic/Capric Triglyceride, Butylene Glycol Dicaprylate/Dicaprate, Glycerin, Neopentyl Glycol Diethylhexanoate, Cetyl Ethylhexanoate, PEG-30 Dipolyhydroxystearate, Pentylene Glycol, Cetyl PEG/PPG-10/1 Dimethicone, Polymethyl Methacrylate, PEG-10 Dimethicone, Cyclopentasiloxane, Phenoxyethanol, Magnesium Sulfate, Sorbitan Isostearate, Beeswax, Stearalkonium Hectorite, Triethoxycaprylylsilane, Aluminum Hydroxide, Stearic Acid, Dimethicone, Ethylhexylglycerin, Disodium EDTA. May Contain: Titanium Dioxide, Iron Oxides, Mica.